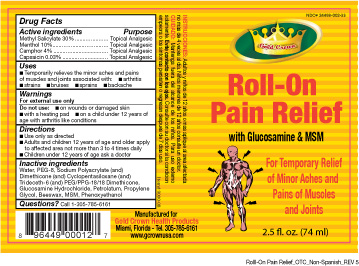 DRUG LABEL: Pain ReliefRoll On
	
NDC: 24488-002 | Form: LIQUID
Manufacturer: Creations Garden Natural Products, Inc. 
Category: otc | Type: HUMAN OTC DRUG LABEL
Date: 20100310

ACTIVE INGREDIENTS: Methyl Salicylate 21 g/70 g; Menthol 7 g/70 g; CAMPHOR, (SYNTHETIC) 2.8 g/70 g
INACTIVE INGREDIENTS: Water; Polyethylene Glycol 400; Glucosamine Hydrochloride; Petrolatum; Propylene Glycol; Wax, Yellow; Dimethyl Sulfone; Phenoxyethanol; Capsaicin

Drug Facts

Active Ingredients

Methyl Salicylate 30% .......….......… Topical Analgesic
Menthol 10% ...……......……….....… Topical Analgesic
Camphor 4% .……..…….............….. Topical Analgesic
Capsaicin 0.03% .……..…….............Topical Analgesic

Uses

■ Temporarily relieves the minor aches and pains of
muscles and joints associated with: ■ arthritis
■ strains ■ bruises ■ sprains ■ backache

Warnings

For external use only

Do not use: ■ on wounds or damaged skin
■ with a heating pad ■ on a child under 12 years of
age with arthritis like conditions

Directions

■ Use only as directed
■ Adults and children 12 years of age and older apply
to affected area not more than 3 to 4 times daily
■ Children under 12 years of age ask a doctor

Inactive ingredients

Water, PEG-8, Sodium Polyacrylate (and) Dimethicone (and) Cyclopentasiloxane (and) Trideceth-6 (and) PEG/PPG-18 Dimethicone, Glucosamine Hydrochloride, Petrolatum, Propylene Glycol, Beeswax, MSM, Phenoxyethanol

Questions?

Questions? Call 1-305-785-6161